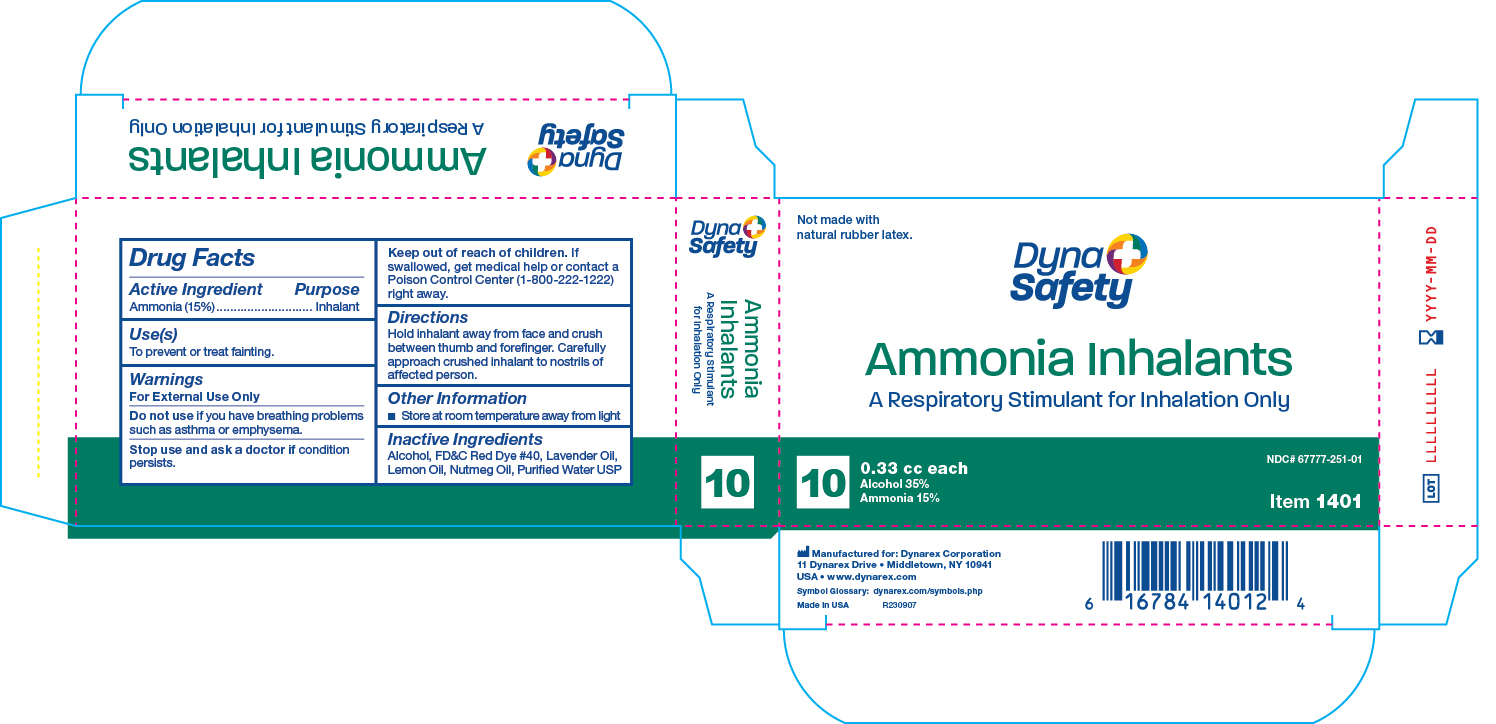 DRUG LABEL: Ammonia Inhalants
NDC: 67777-251 | Form: INHALANT
Manufacturer: Dynarex Corporation
Category: otc | Type: HUMAN OTC DRUG LABEL
Date: 20250811

ACTIVE INGREDIENTS: AMMONIA 0.05 g/0.33 mL
INACTIVE INGREDIENTS: ALCOHOL

1401 Ammonia Inhalants (Ampule) NDC 67777-251-01

active ingredient each inhalant purpose ammonia 15% inhalant

PURPOSE

Uses to prevent or treating fainting

warnings for external use only

do not use if you have breathing problems such as asthma or emphysema

stop use and ask a doctor if condition persists

KEEP OUT OF REACH OF CHILDREN

If swallowed get medical help or contact a Poison Control Center right away

DOSAGE AND ADMINISTRATION

Hold inhalant away from face and crush between thumb and forefinger. carefully approach crushed inhalant to nostrils of affected person.

STORAGE AND HANDLING

Store at room temperature away from light

INACTIVE INGREDIENT

alcohol fdc red dye 40 lavender oil, lemon oil, nutmeg oil, purified water usp

INDICATIONS AND USAGE

to prevent or treat fainting

WARNINGS

for external use only

Label

1401 Ammonia Inhalants